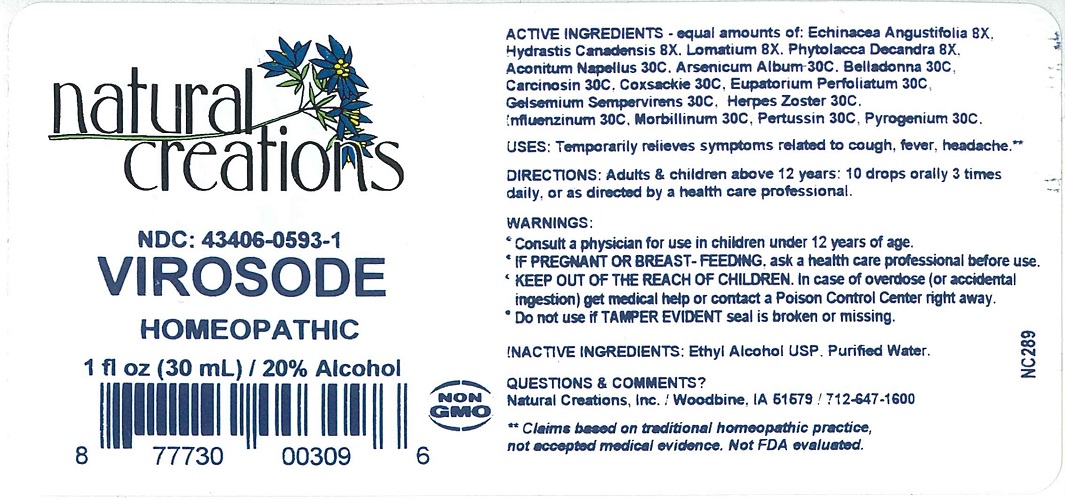 DRUG LABEL: VIROSODE
NDC: 43406-0593 | Form: LIQUID
Manufacturer: Natural Creations, Inc
Category: homeopathic | Type: HUMAN OTC DRUG LABEL
Date: 20251218

ACTIVE INGREDIENTS: ECHINACEA ANGUSTIFOLIA 8 [hp_X]/1 mL; GOLDENSEAL 8 [hp_X]/1 mL; LOMATIUM DISSECTUM WHOLE 8 [hp_X]/1 mL; PHYTOLACCA AMERICANA ROOT 8 [hp_X]/1 mL; ACONITUM NAPELLUS 30 [hp_C]/1 mL; ARSENIC TRIOXIDE 30 [hp_C]/1 mL; ATROPA BELLADONNA 30 [hp_C]/1 mL; HUMAN BREAST TUMOR CELL 30 [hp_C]/1 mL; HUMAN COXSACKIEVIRUS A 30 [hp_C]/1 mL; EUPATORIUM PERFOLIATUM FLOWERING TOP 30 [hp_C]/1 mL; GELSEMIUM SEMPERVIRENS ROOT 30 [hp_C]/1 mL; HUMAN HERPESVIRUS 3 30 [hp_C]/1 mL; INFLUENZA A VIRUS A/SINGAPORE/GP1908/2015 IVR-180 (H1N1) WHOLE 30 [hp_C]/1 mL; INFLUENZA A VIRUS A/NORTH CAROLINA/04/2016 (H3N2) WHOLE 30 [hp_C]/1 mL; INFLUENZA B VIRUS B/IOWA/06/2017 WHOLE 30 [hp_C]/1 mL; INFLUENZA B VIRUS B/SINGAPORE/INFTT-16-0610/2016 WHOLE 30 [hp_C]/1 mL; MEASLES VIRUS 30 [hp_C]/1 mL; HUMAN SPUTUM, BORDETELLA PERTUSSIS INFECTED 30 [hp_C]/1 mL; RANCID BEEF 30 [hp_C]/1 mL
INACTIVE INGREDIENTS: ALCOHOL; WATER

VIROSODE

ACTIVE INGREDIENT

ACTIVE INGREDIENTS - equal amounts of: Echinacea Angustifolia 8X, Hydrastis Canadensis 8X, Lomatium 8X, Phytolacca Decandra 8X, Aconitum Napellus 30C, Arsenicum Album 30C, Belladonna 30C, Carcinosin 30C, Coxsackie 30C, Eupatorium Perfoliatium 30C, Gelsemium Sempervirens 30C, Herpes Zoster 30C, Influenzinum 30C, Morbillinum 30C, Pertussin 30C, Pyrogenium 30C.

INDICATIONS AND USAGE

USES: Temporarily relieves symptoms related to cough, fever, headache.**

PURPOSE

USES: Temporarily relieves symptoms related to cough, fever, headache.**

DOSAGE AND ADMINISTRATION

DIRECTIONS: Adults & children above 12 years: 10 drops orally 3 times daily, or as directed by a health care professional.

KEEP OUT OF REACH OF CHILDREN

KEEP OUT OF THE REACH OF CHILDREN. In case of overdose (or accidental ingestion) get medical help or contact a Poison Control Center right away.

WARNINGS:

- Consult a physician for use in children under 12 years of age.
- IF PREGNANT OR BREAST-FEEDING, ask a health care professional before use.
- KEEP OUT OF THE REACH OF CHILDREN. In case of overdose (or accidental ingestion) get medical help or contact a Poison Control Center right away.
- Do not use if TAMPER EVIDENT seal is broken or missing.

INACTIVE INGREDIENTS: Ethyl Alcohol USP, Purified Water.

QUESTIONS & COMMENTS?

Natural Creations, Inc. / Woodbine, IA 51579 / 712-647-1600

REFERENCES

**Claims based on traditional homeopathic practice, not accepted medical evidence. Not FDA evaluated.

PACKAGE LABEL

NDC: 43406-0593-1

Virosode

Homeopathic

1 fl oz (30 mL) / 20% Alcohol